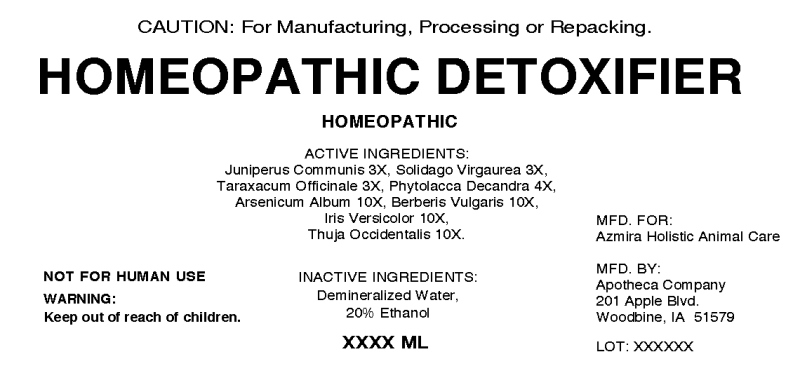 DRUG LABEL: Homeopathic Detoxifier
NDC: 57520-1365 | Form: LIQUID
Manufacturer: Apotheca Company
Category: other | Type: BULK INGREDIENT - ANIMAL DRUG
Date: 20201016

ACTIVE INGREDIENTS: JUNIPER BERRY 3 [hp_X]/1 mL; SOLIDAGO VIRGAUREA FLOWERING TOP 3 [hp_X]/1 mL; TARAXACUM OFFICINALE 3 [hp_X]/1 mL; PHYTOLACCA AMERICANA ROOT 4 [hp_X]/1 mL; ARSENIC TRIOXIDE 10 [hp_X]/1 mL; BERBERIS VULGARIS ROOT BARK 10 [hp_X]/1 mL; IRIS VERSICOLOR ROOT 10 [hp_X]/1 mL; THUJA OCCIDENTALIS LEAFY TWIG 10 [hp_X]/1 mL
INACTIVE INGREDIENTS: WATER; ALCOHOL

Drug Facts:

ACTIVE INGREDIENTS:

Juniperus Communis 3X, Solidago Virgaurea 3X, Taraxacum Officinale 3X, Phytolacca Decandra 4X, Arsenicum Album 10X, Berberis Vulgaris 10X, Iris Versicolor 10X, Thuja Occidentalis 10X.

PURPOSE:

CAUTION: For Manufacturing, Processing or Repacking.

WARNINGS:

Keep out of reach of children.

NOT FOR HUMAN USE

Keep out of reach of children. In case of overdose, contact physician or Poison Control Center right away.

DIRECTIONS:

TO BE DETERMINED BY FINAL PROCESSOR

INDICATIONS:

TO BE DETERMINED BY FINAL PROCESSOR

INACTIVE INGREDIENTS:

Demineralized Water, 20% Ethanol

QUESTIONS:

MFD: FOR:

Azmira Holistic Animal Care

MFD. BY:

Apotheca Company

201 Apple Blvd.

Woodbine, IA 51579

PACKAGE LABEL DISPLAY:

CAUTION: For manufacturing, processing or repacking.

HOMEOPATHIC DETOXIFIER

HOMEOPATHIC